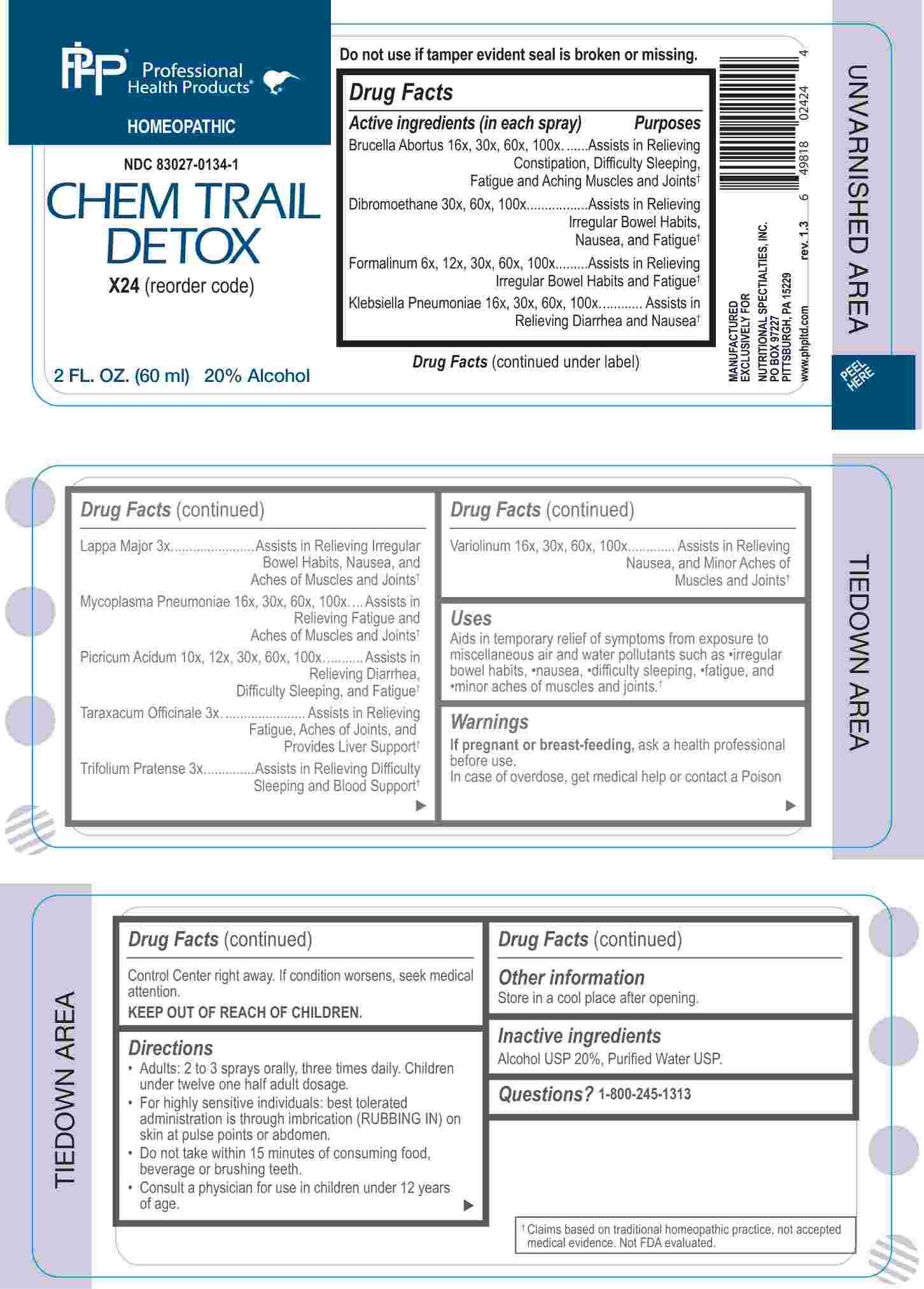 DRUG LABEL: Chem Trail Detox
NDC: 83027-0134 | Form: SPRAY
Manufacturer: Nutritional Specialties, Inc.
Category: homeopathic | Type: HUMAN OTC DRUG LABEL
Date: 20250407

ACTIVE INGREDIENTS: ARCTIUM LAPPA ROOT 3 [hp_X]/1 mL; TARAXACUM OFFICINALE 3 [hp_X]/1 mL; TRIFOLIUM PRATENSE FLOWER 3 [hp_X]/1 mL; FORMALDEHYDE SOLUTION 6 [hp_X]/1 mL; PICRIC ACID 10 [hp_X]/1 mL; BRUCELLA ABORTUS 16 [hp_X]/1 mL; KLEBSIELLA PNEUMONIAE 16 [hp_X]/1 mL; MYCOPLASMA PNEUMONIAE 16 [hp_X]/1 mL; VARIOLA VIRUS 16 [hp_X]/1 mL; ETHYLENE DIBROMIDE 30 [hp_X]/1 mL
INACTIVE INGREDIENTS: WATER; ALCOHOL

DRUG FACTS:

ACTIVE INGREDIENTS:

Brucella Abortus 16X, 30X, 60X, 100X, Dibromoethane 30X, 60X, 100X, Formalinum 6X, 12X, 30X, 60X, 100X, Klebsiella Pneumoniae 16X, 30X, 60X, 100X, Lappa Major 3X, Mycoplasma Pneumoniae 16X, 30X, 60X, 100X, Picricum Acidum 10X, 12X, 30X, 60X, 100X, Taraxacum Officinale 3X, Trifolium Pratense 3X, Variolinum 16X, 30X, 60X, 100X.

PURPOSE:

Brucella Abortus – Assists in Relieving Constipation, Difficulty Sleeping, Fatigue and Aching Muscles and Joints,† Dibromoethane – Assists in Relieving Irregular Bowel Habits, Nausea, and Fatigue,† Formalinum – Assists in Relieving Irregular Bowel Habits and Fatigue,† Klebsiella Pneumoniae – Assists in Relieving Diarrhea and Nausea,† Lappa Major – Assists in Relieving Irregular Bowel Habits, Nausea, and Aches of Muscles and Joints,† Mycoplasma Pneumoniae – Relieving Fatigue and Aches of Muscles and Joints,† Picricum Acidum – Assists in Relieving Diarrhea, Difficulty Sleeping, and Fatigue,† Taraxacum Officinale – Assists in Relieving Fatigue, Aches of Joints, and Provides Liver Support,† Trifolium Pratense – Assists in Relieving Difficulty Sleeping and Blood Support,† Variolinum – Assists in Relieving Nausea, and Minor Aches of Muscles and Joints†

†Claims based on traditional homeopathic practice, not accepted medical evidence. Not FDA evaluated.

USES:

Aids in temporary relief of symptoms from exposure to miscellaneous air and water pollutants such as irregular bowel habits, nausea, difficulty sleeping, fatigue, and minor aches of muscles and joints.†

†Claims based on traditional homeopathic practice, not accepted medical evidence. Not FDA evaluated.

WARNINGS:

If pregnant or breast-feeding, ask a health professional before use.

In case of overdose, get medical help or contact a Poison Control Center right away.

If condition worsens, seek medical attention.

KEEP OUT OF REACH OF CHILDREN

Do not use if tamper evident seal is broken or missing.

Store in a cool place after opening

KEEP OUT OF REACH OF CHILDREN:

In case of overdose, get medical help or contact a Poison Control Center right away.

DIRECTIONS:

• Adults: 2 to 3 sprays orally, three times daily. Children under twelve one half adult dosage.

• For highly sensitive individuals: best tolerated administration is through imbrication (RUBBING IN) on skin at pulse points or abdomen.

• Do not take within 15 minutes of consuming food, beverage or brushing teeth.

Consult a physician for use in children under 12 years of age.

INACTIVE INGREDIENTS:

Alcohol USP 20%, Purified Water USP.

QUESTIONS:

MANUFACTURED EXCLUSIVELY FOR

NUTRITIONAL SPECIALTIES, INC.

PO BOX 97227

PITTSBURG, PA 15229

www.phpltd.com

1-800-245-1313

PACKAGE LABEL DISPLAY:

Professional

Health Products

HOMEOPATHIC

NDC 83027-0134-1

CHEM TRAIL

DETOX

2 FL. OZ (60 ml)